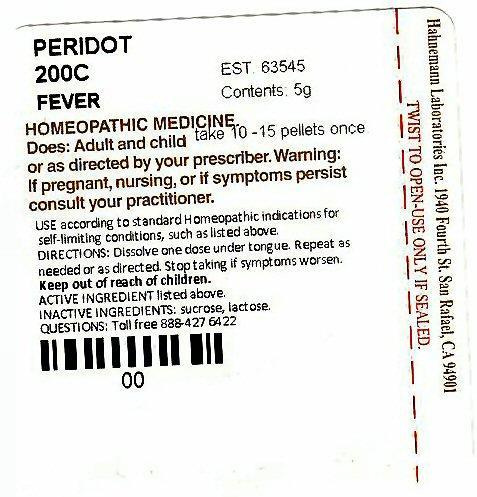 DRUG LABEL: HAHNEMANN FEVER
NDC: 63545-639 | Form: PELLET
Manufacturer: Hahnemann Laboratories, Inc. dba Alpine Pharmaceuticals
Category: homeopathic | Type: HUMAN OTC DRUG LABEL
Date: 20120114

ACTIVE INGREDIENTS: OLIVINE 200 [hp_C]/1 1
INACTIVE INGREDIENTS: SUCROSE; LACTOSE

Active Ingredient

ACTIVE INGREDIENT listed above

PERIDOT

Purpose

FEVER

Keep Out Of Reach Of Children

Use

USE according to standard Homeopathic indications for self-limiting conditions, such as listed above. FEVER

Warnings

Warning: If pregnant, nursing, or if symptoms persist consult your practitioner.

Directions

DIRECTIONS: Dissolve one dose under tongue. Repeat as needed or as directed. Stop taking if symptoms worsen.
DOSE: Adults and children take 10 -15 pellets once or as directed by your prescriber.

Inactive Ingredients

INACTIVE INGREDIENTS: sucrose. lactose

Package Label

PERIDOT 200C FEVER EST 63545 Contains 5g
HOMEOPATHIC MEDICINE
Hahnemann Laboratories Inc. 1940 Fourth St. San Rafael, CA 94901
TWIST TO OPEN-USE ONLY IF SEALED
QUESTIONS: Toll free 888-427-6422